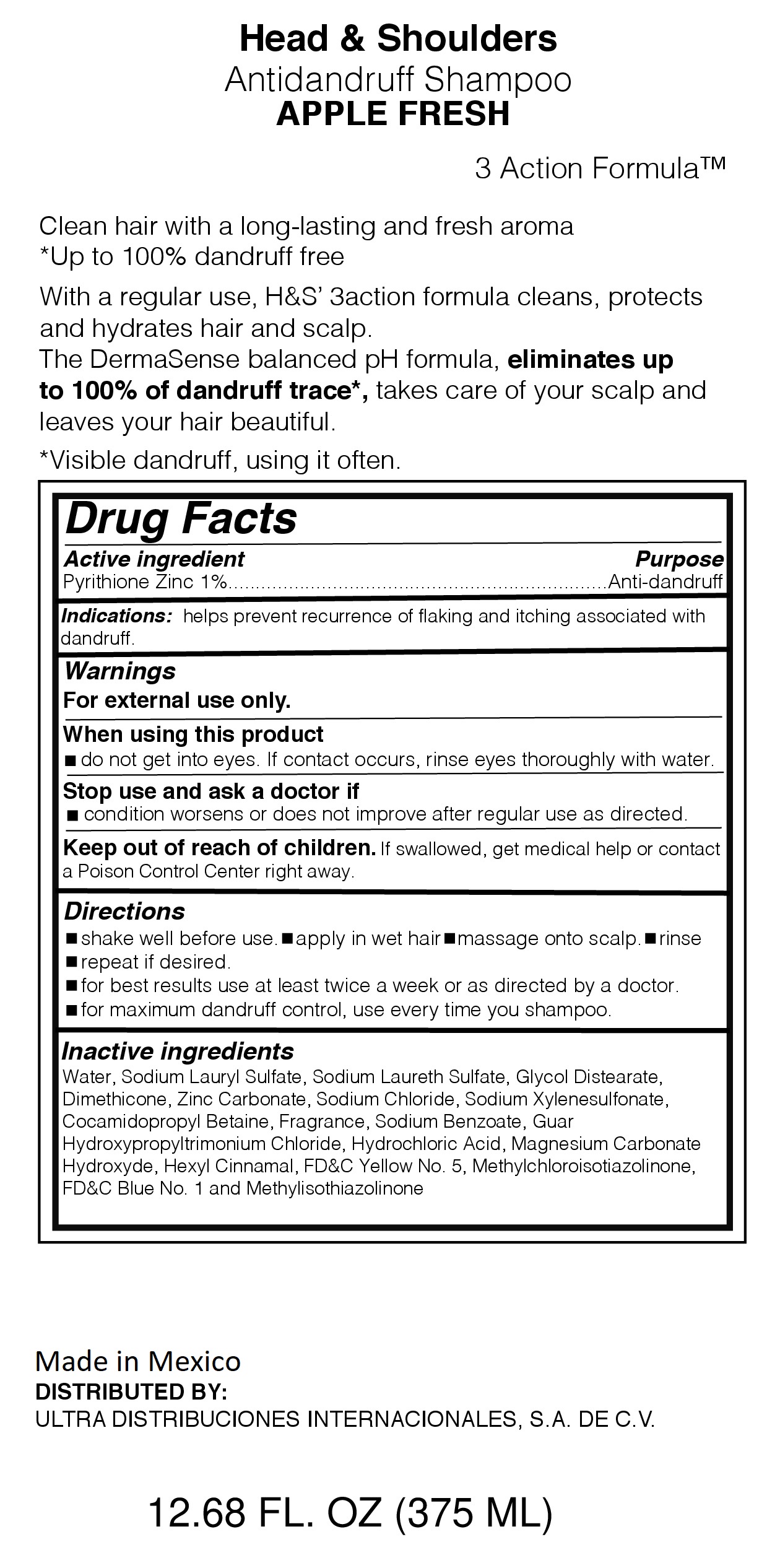 DRUG LABEL: HEAD AND SHOULDERS APPLE FRESH
NDC: 72389-104 | Form: LOTION/SHAMPOO
Manufacturer: ULTRA DISTRIBUCIONES INTERNACIONALES, S.A. DE C.V.
Category: otc | Type: HUMAN OTC DRUG LABEL
Date: 20220114

ACTIVE INGREDIENTS: PYRITHIONE ZINC 1 g/100 mL
INACTIVE INGREDIENTS: WATER; SODIUM LAURYL SULFATE; SODIUM LAURETH SULFATE; GLYCOL DISTEARATE; MAGNESIUM CARBONATE HYDROXIDE; DIMETHICONE; SODIUM CHLORIDE; SODIUM XYLENESULFONATE; COCAMIDOPROPYL BETAINE; METHYLISOTHIAZOLINONE; SODIUM BENZOATE; GUAR HYDROXYPROPYLTRIMONIUM CHLORIDE (1.7 SUBSTITUENTS PER SACCHARIDE); HYDROCHLORIC ACID; ZINC CARBONATE; METHYLCHLOROISOTHIAZOLINONE; FD&C BLUE NO. 1; .ALPHA.-HEXYLCINNAMALDEHYDE; FD&C YELLOW NO. 5

Head and Shoulders Apple Fresh

Purpose

Clean hair with a long-lasting and fresh aroma

*Up to 100% dandruff free

With Regular use, H&S 3action formula cleans, protects and hydrates hair and scalf.

The DermaSense balanced pH formula, eliminates up to 100% of dandruff trace*, takes care of your scalp and leaves your hair

beautiful,

*Visible dandruff, using it often.

Active Ingredient

Active Ingredient................................................................................Purpose

Pyrithione Zinc 1%.....................................................................Anti-dandruff

Warnings

for external use only.

When using this product

-do not get into eyes. If contact occurs, rinse thoroughly with water

Stop use and ask doctor if

condition worsens or does not improve after regular use as directed

Keep our of reach of children

If swallowed, get medical help or contact a Poison Control Center right away

Directions

-shake well before use - apply in wet hair - massage into scalp - rinse

-repeat as desired

-for best results use at least twice a week or as directed by a doctor

-for maximum dandruff control, use every time you shampoo

Inactive Ingredients

Water, Sodium Lauryl Sulfate, Sodium Laureth Sulfate, Glycol Distearate,

Dimethicone, Zinc Carbonate, Sodium Chloride, Sodium Xylenesulfonate,

Cocamidopropyl Betaine, Fragrance, Sodium Benzoate, Guar

Hydroxypropyltrimonium Chloride, Hydrochloric Acid,

Magnesium Carbonate Hydroxide, Hexyl Cinnamal, FD&C Yellow No. 5, Methylchloroisothiazolinone,

FD&C Blue 1 and Methylisothiaolinone,

Distributed by:

ULTRA DISTRIBUCIONES INTERNACIONALES, S.A. DE C.V.

Made in Mexico

Indications:

helps prevent recurrence of flaking and itching associated with dandruff

Principal Display Panel Antidandruff Shampoo APPLE FRESH

APPLE FRESH